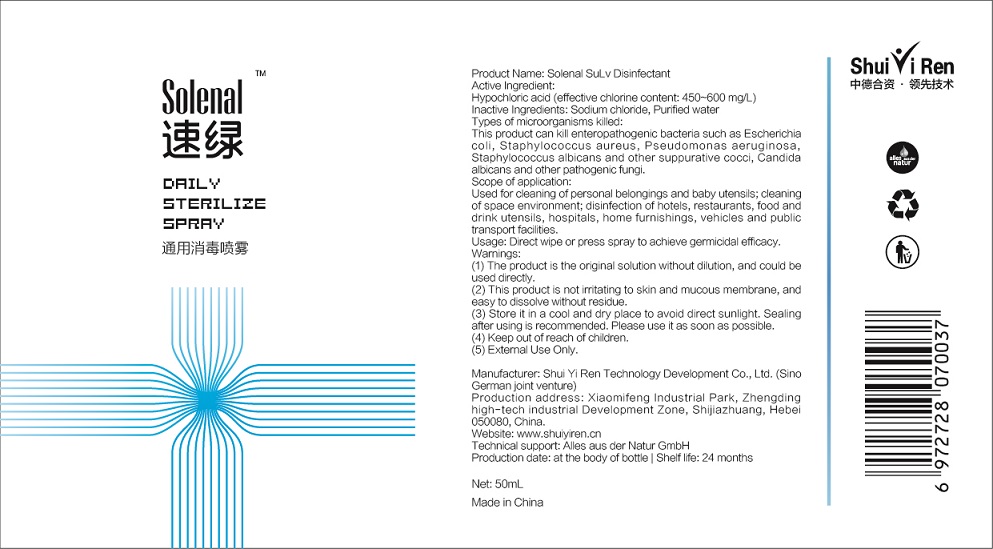 DRUG LABEL: Solenal SuLv Disinfectant
NDC: 76761-101 | Form: LIQUID
Manufacturer: Shui Yi Ren Technology Development Co., Ltd.
Category: otc | Type: HUMAN OTC DRUG LABEL
Date: 20200523

ACTIVE INGREDIENTS: HYPOCHLOROUS ACID 776.9 mg/1000 mL
INACTIVE INGREDIENTS: SODIUM CHLORIDE; WATER

ShuiYiRen, Disinfectant, Liquid-Spray

Active Ingredient(s)

Hypochlorous Acid: 776.9 mg/L. Purpose: Kill microorganism.

Purpose

This product can kill enteropathogenic bacteria such as Escherichia coli, Staphylococcus aureus, Pseudomonas aeruginosa, Staphylococcus albicans and other suppurative cocci, Candida albicans and other pathogenic fungi.

Use

Used for cleaning of personal belongings and baby utensils; cleaning of space environment; disinfection of hotels, restaurants, food and drink utensils, hospitals, home furnishings, vehicles and public transport facilities.

Warnings

(1) The product is the original solution without dilution, and could be used directly.

(2) This product is not irritating to skin and mucous membrane, and easy to dissolve without residue.

(3) Store it in a cool and dry place to avoid direct sunlight. Sealing after using is recommended. Please use it as soon as possible.

(4) Keep out of reach of children.

(5) External Use Only.

Do not use

- on open skin wounds
- mixing this product with other disinfectants

When using:

- The product is the original solution without dilution, and could be used directly.
- This product is not irritating to skin and mucous membrane, and easy to dissolve without residue.

Stop use and ask a doctor if irritation or rash occurs. These may be signs of a serious condition.

Keep out of reach of children.

Directions

Direct wipe or press spray to achieve germicidal efficacy.

Other information

Store it in a cool and dry place to avoid direct sunlight. Sealing after using is recommended. Please use it as soon as possible.

Inactive ingredients

Sodium chloride, Purified water